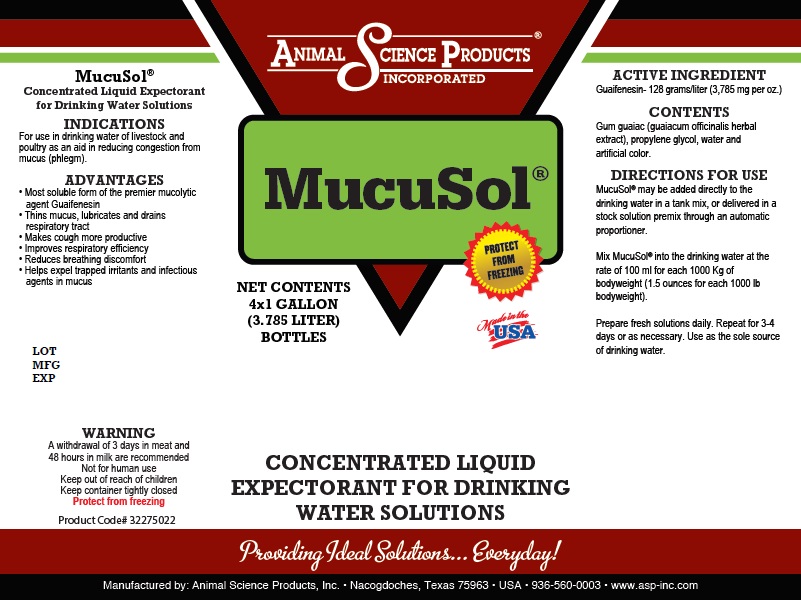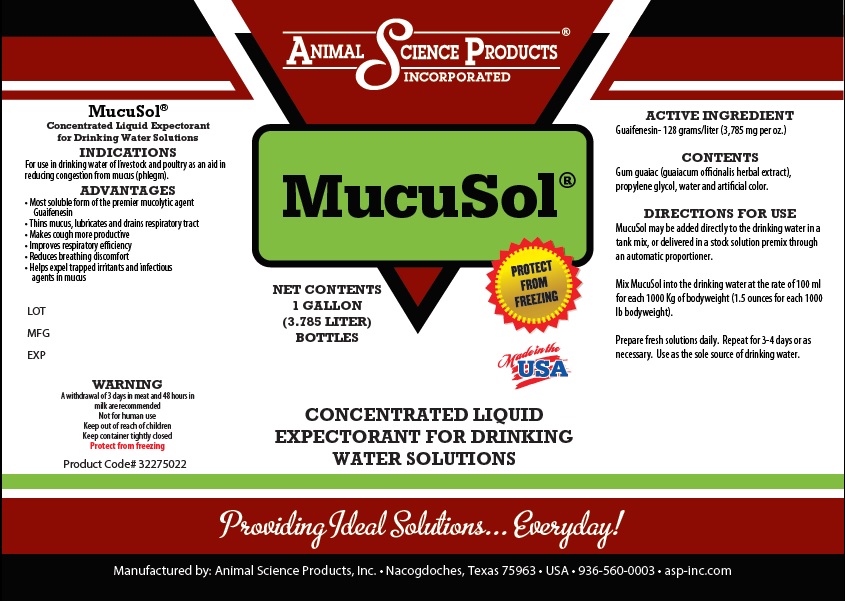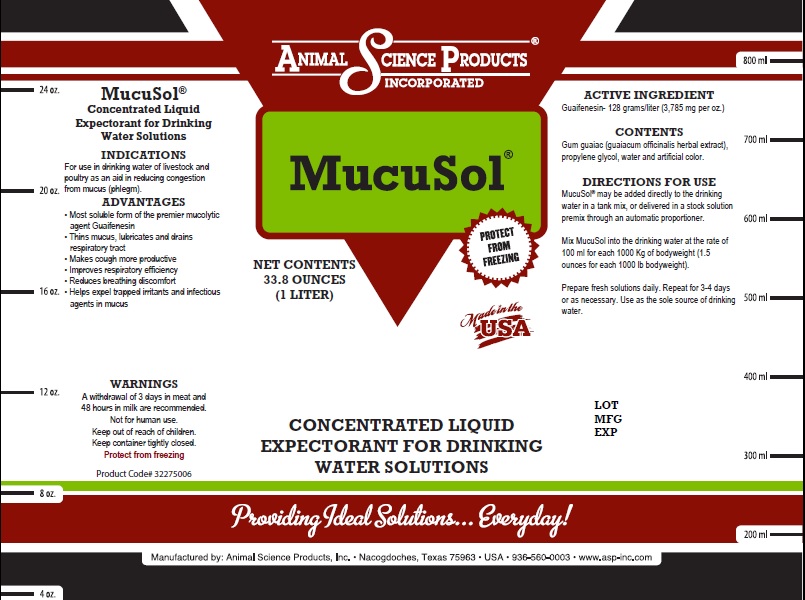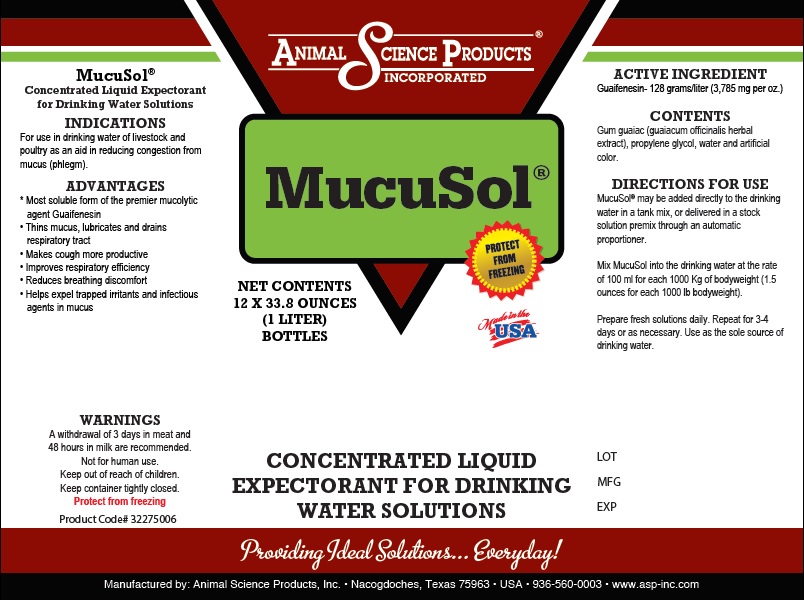 DRUG LABEL: MUCUSOL
NDC: 57932-004 | Form: LIQUID
Manufacturer: Animal Science Products Inc
Category: animal | Type: OTC ANIMAL DRUG LABEL
Date: 20251028

ACTIVE INGREDIENTS: GUAIFENESIN 128 g/1 L
INACTIVE INGREDIENTS: PROPYLENE GLYCOL; WATER; FD&C YELLOW NO. 5; FD&C BLUE NO. 1; GUAIACUM OFFICINALE RESIN

MucuSol

Active ingredient

Guaifenesin- 128 grams/liter (3,785 mg per ounce)

Directions for Use

MucuSol may be added directly to the drinking water in a tank mix, or delivered in a stock solution premix through an automatic proportioner.

Mix MucuSol into the drinking water at the rate of 100 ml for each 1000 kg of bodyweight (1.5 ounces for each 1000 Ib bodyweight).

Prepare fresh solutions daily. Repeat for 3-4 days or as necessary. Use as the sole source of drinking water.

Indications

For use in the drinking water of live stock and poultry as an aid in reducing congestion from mucus (phlegm)

PURPOSE

Advantages

• Most soluble form of the premier mucolytic agent Guaifenesin

• Thins mucus, lubricates and drains respiratory tract

• Makes cough more productive

• Improves respiratory efficiency

• Reduces breathing discomfort

• Helps expel trapped irritants and infectious agents in mucus

Warning

A withdrawal of 3 days in meat and 48 hours in milk are recommended

Not for human use

Keep out of reach of children

Keep container tightly closed

Protect from freezing

Excipients

Gum guaiac (guaiacum officinalis herbal extract), propylene glycol, water and artificial color